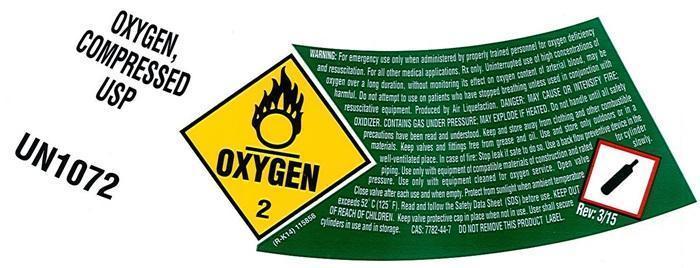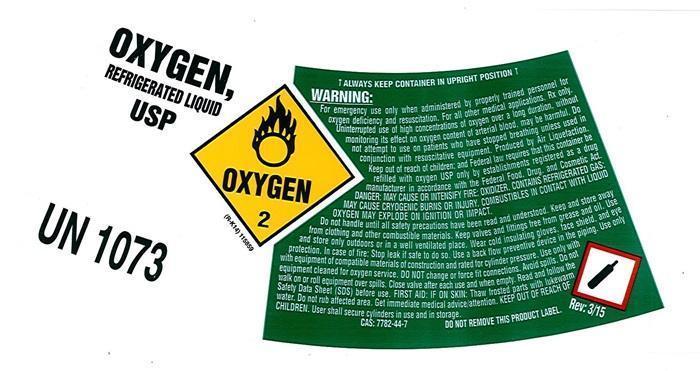 DRUG LABEL: OXYGEN
NDC: 64650-345 | Form: GAS
Manufacturer: Airweld, Inc.
Category: prescription | Type: HUMAN PRESCRIPTION DRUG LABEL
Date: 20241008

ACTIVE INGREDIENTS: OXYGEN 99 L/100 L

Oxygen

OXYGEN COMPRESSED LABEL

OXYGEN, COMPRESSED USP UN 1072 OXYGEN 2 (R-K14) 115856

WARNING: For emergency use only when administered by properly trained personnel for oxygen deficiency and resuscitation. For all other medical applications, Rx only. Uninterrupted use of high concentrations of oxygen over a long duration, without monitoring its effect on oxygen content of arterial blood, may be harmful. Do not attempt to use on patients who have stopped breathing unless used in conjunction with resuscitative equipment. Produced by Air Liquefaction. DANGER: MAY CAUSE OR INTENSIFY FIRE; OXIDIZER. CONTAINS GAS UNDER PRESSURE; MAY EXPLODE IF HEATED. Do not handle until all safety precautions have been read and understood. Keep and store away from clothing and other combustible materials. Keep valves and fittings free from grease and oil. Use and store only outdoors or in a well-ventilated place. In case of fire: Stop leak if safe to do so. Use a back flow preventive device in the piping. Use only with equipment of compatible materials of construction and rated for cylinder pressure. Use only with equipment cleaned for oxygen service. Open valve slowly. Close valve after each use and when empty. Protect from sunlight when ambient temperature exceeds 52°C (125° F). Read and follow the Safety Data Sheet (SDS) before use. CAS 7782-44-7 DO NOT REMOVE THIS PRODUCT LABEL.

Rev: 3/15

Oxygen Liquid

OXYGEN, REFRIGERATED LIQUID USP UN1073

OXYGEN 2 (R-K14) 115859

! ALWAYS KEEP CONTAINER IN UPRIGHT POSITION.!

DO NOT CHANGE OR FORCE FIT CONNECTINS.

WARNING: For emergency use only when administered by properly trained personnel for oxygen deficiency and resuscitation. For all other medical applications, Rx only.

Uninterrupted use of high concentrations of oxygen over a long duration, without monitoring its effect on oxygen content of arterial blood, may be harmful. Do not attempt to use on patients who have stopped breathing unless used in conjunction of resuscitative equipment.

Produced by Air Liquefaction.

WARNING: EXTREMELY COLD, OXIDIZING LIQUID AND GAS UNDER PRESSURE. VIGOROUSLY ACCLERATES COMBUSION. COMBUSTIBLES IN CONTACT WITH LIQUID OXYGEN MAY EXPLODE ON IGNITIN OR IMPACT. CAN CAUSE SEVERE FROSTBITE.

Keep oil, grease, and combustibles away. Use only with equipment cleaned for oxygen service. Store and use with adequate ventilation. Do not get liquid in eyes, on skin, or clothing. For liquid withdrawal, wear face shield and gloves. Do not drop. Use suitable hand truck for container movement. Avoid spills. Do not walk on or roll equipment over spills. Cylinder temperature should not exceed 52°C (125°F). Close valve after each use and when empty. Use a back flow preventive device in the piping. Use in accordance with the Material Safety Data Sheet (MSDS).

FIRST AID FIRST AID: IN CASE OF FROSTBITE, obtain medical treatment immediately.

CAS: 7782-44-7

DO NOT REMOVE THIS PRODUCT LABEL

Rev: 3/15